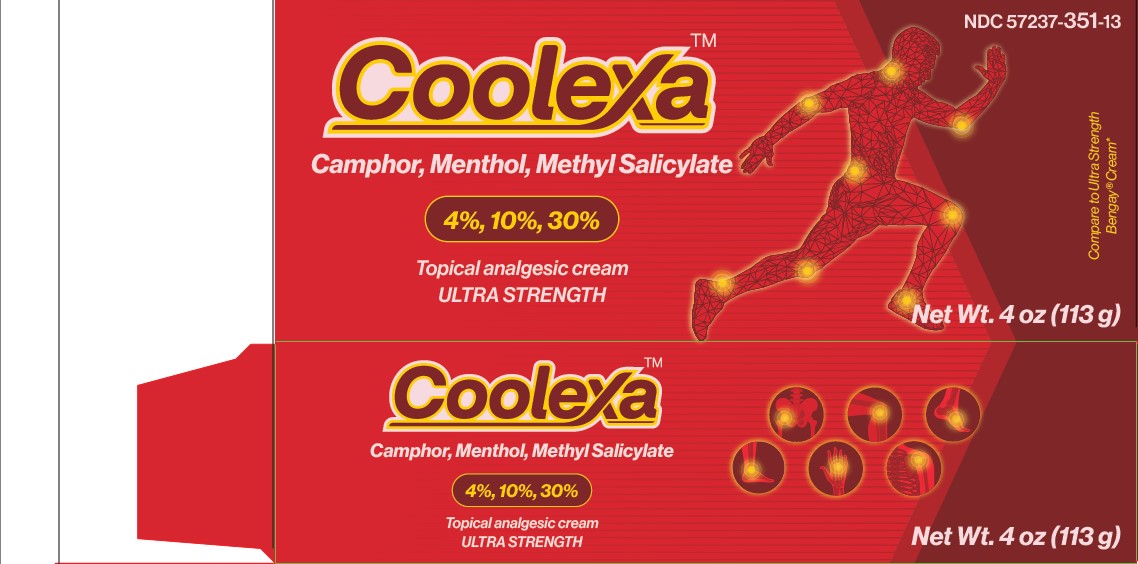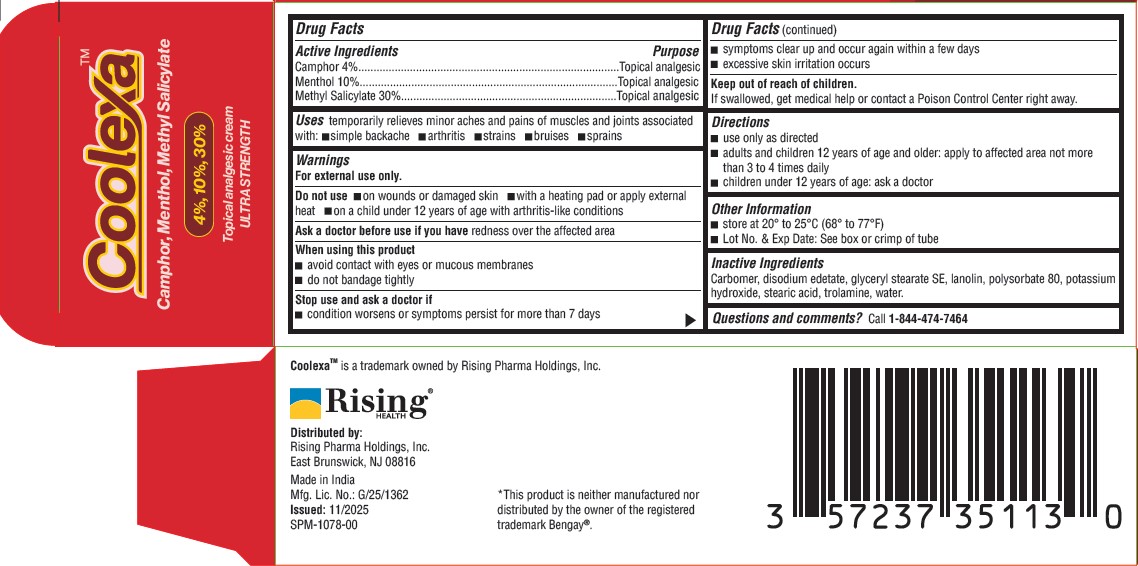 DRUG LABEL: Coolexa
NDC: 57237-351 | Form: CREAM
Manufacturer: Rising Pharma Holdings, Inc.
Category: otc | Type: HUMAN OTC DRUG LABEL
Date: 20251106

ACTIVE INGREDIENTS: CAMPHOR (SYNTHETIC) 40 mg/1 g; MENTHOL, UNSPECIFIED FORM 100 mg/1 g; METHYL SALICYLATE 300 mg/1 g
INACTIVE INGREDIENTS: CARBOMER; EDETATE DISODIUM; GLYCERYL STEARATE SE; LANOLIN; POLYSORBATE 80; POTASSIUM HYDROXIDE; STEARIC ACID; TROLAMINE; WATER

Camphor 4%, Menthol 10%, Methyl Salicylate 30%
Topical analgesic cream
ULTRA STRENGTH

Drug Facts

ACTIVE INGREDIENT

Active Ingredients | Purpose
Camphor 4% | Topical analgesic
Menthol 10% | Topical analgesic
Methyl Salicylate 30% | Topical analgesic

Uses

temporarily relieves minor aches and pains of muscles and joints associated with:

- simple backache
- arthritis
- strains
- bruises
- sprains

Warnings

For external use only.

Do not use

- on wounds or damaged skin
- with a heating pad or apply external heat
- on a child under 12 years of age with arthritis-like conditions

Ask a doctor before use if you have redness over the affected area

When using this product

- avoid contact with eyes or mucous membranes
- do not bandage tightly

Stop use and ask a doctor if

- condition worsens or symptoms persist for more than 7 days
- symptoms clear up and occur again within a few days
- excessive skin irritation occurs

Keep out of reach of children.

If swallowed, get medical help or contact a Poison Control Center right away.

Directions

- use only as directed
- adults and children 12 years of age and older: apply to affected area not more than 3 to 4 times daily
- children under 12 years of age: ask a doctor

Other Information

- store at 20° to 25°C (68° to 77°F)
- Lot No. & Exp Date: See box or crimp of tube

Inactive Ingredients

Carbomer, disodium edetate, glyceryl stearate SE, lanolin, polysorbate 80, potassium hydroxide, stearic acid, trolamine, water.

Questions and comments?

Call 1-844-474-7464

CoolexaTM is a trademark owned by Rising Pharma Holdings, Inc.

Distributed by:
Rising Pharma Holdings, Inc.
East Brunswick, NJ 08816
Made in India
Mfg. Lic. No.: G/25/1362

PRINCIPAL DISPLAY PANEL - 113 g Tube Carton

Coolexa TM

Camphor, Menthol, Methyl Salicylate

4%, 10%, 30%

Topical analgesic cream

ULTRA STRENGTH

Net Wt. 4 oz (113 g)